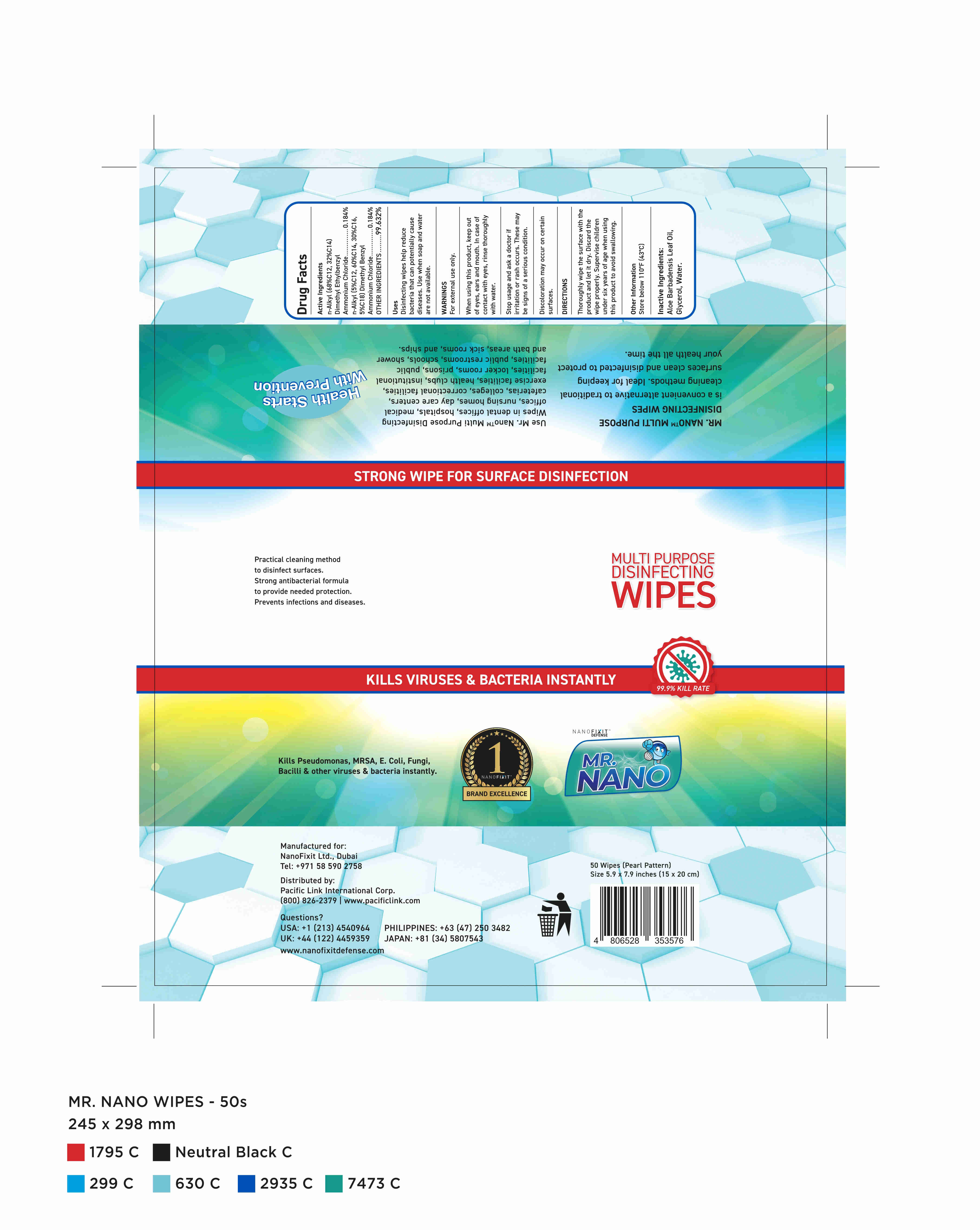 DRUG LABEL: Disinfecting Wipes
NDC: 92763-018 | Form: CLOTH
Manufacturer: NANOFIXIT VENTURES INC.	
Category: otc | Type: HUMAN OTC DRUG LABEL
Date: 20201019

ACTIVE INGREDIENTS: N-ALKYL ETHYLBENZYL DIMETHYL AMMONIUM CHLORIDE (C12-C14) 1 g/50 1; N-ALKYL DIMETHYL BENZYL AMMONIUM CHLORIDE (C12-C18) 1 g/50 1
INACTIVE INGREDIENTS: GREEN TEA LEAF; WATER; PHENOXYETHANOL; PROPYLENE GLYCOL

DOSAGE AND ADMINISTRATION

Store below 110°F(43°C)

INACTIVE INGREDIENT

AQUA

PROPYLENE GLYCOL

PHENOXYETHANOL

GREEN TEA EXTRACT

INDICATIONS AND USAGE

Thoroughly wipe the surface with the product and let it dry. Discardthe wipe properly. Supervise children under six years of age whenusing this product to avoid swallowing.

ACTIVE INGREDIENT

n-Alkyl(68%C12,32%C14) dimethyl ethylbenzyl ammonium chloride

n-Alkyl(5%C12,60%C14,30%C16,5%C18) dimethyl benzyl ammonium chloride

keep out of reach of children

PURPOSE

Disinfection
Sterilization
No Rinseing

WARNINGS

For external use only.When using this product, keep out of eyes,ears and mouth. In case of contact with eyes, rinse eyes thoroughly with water.